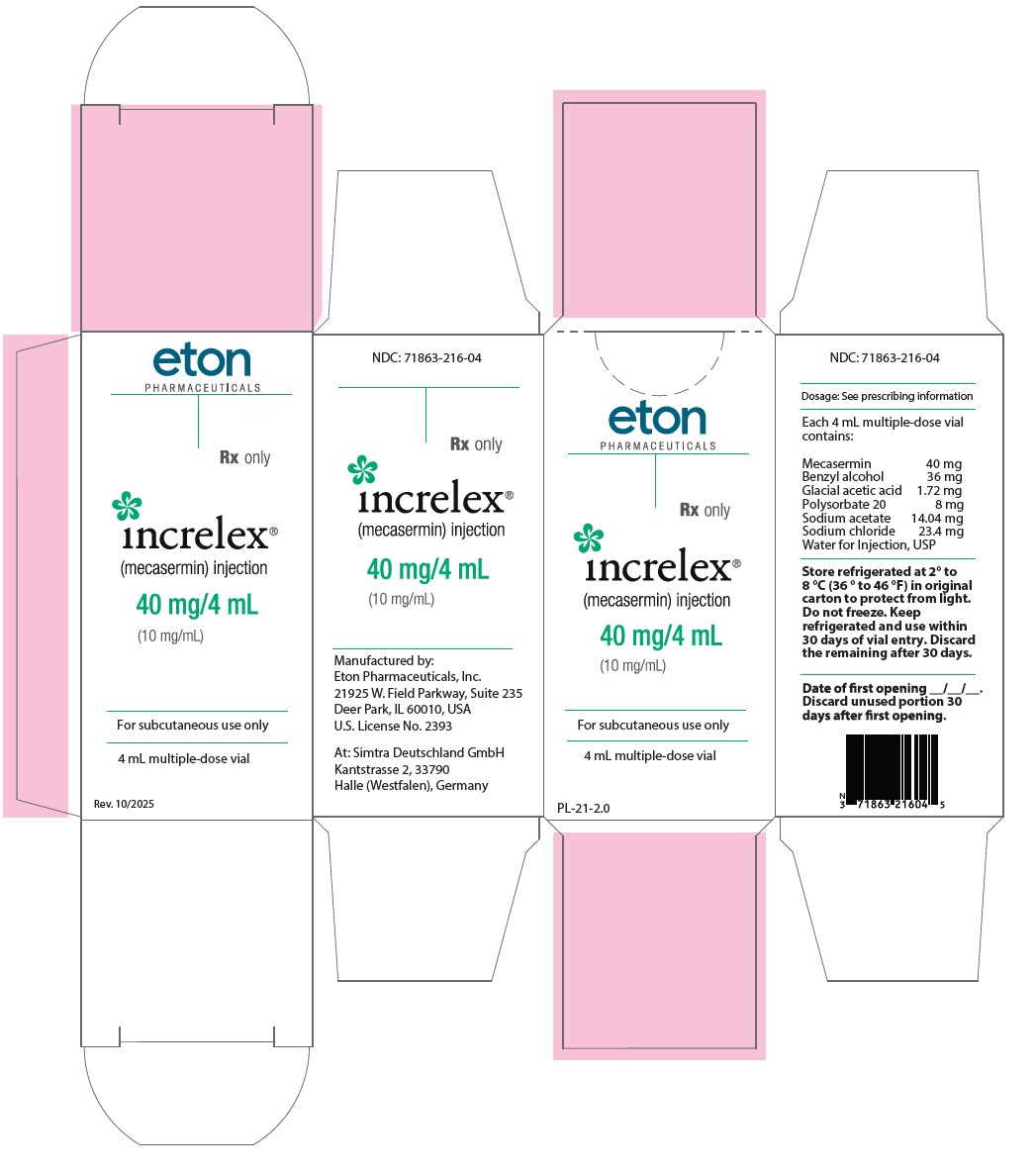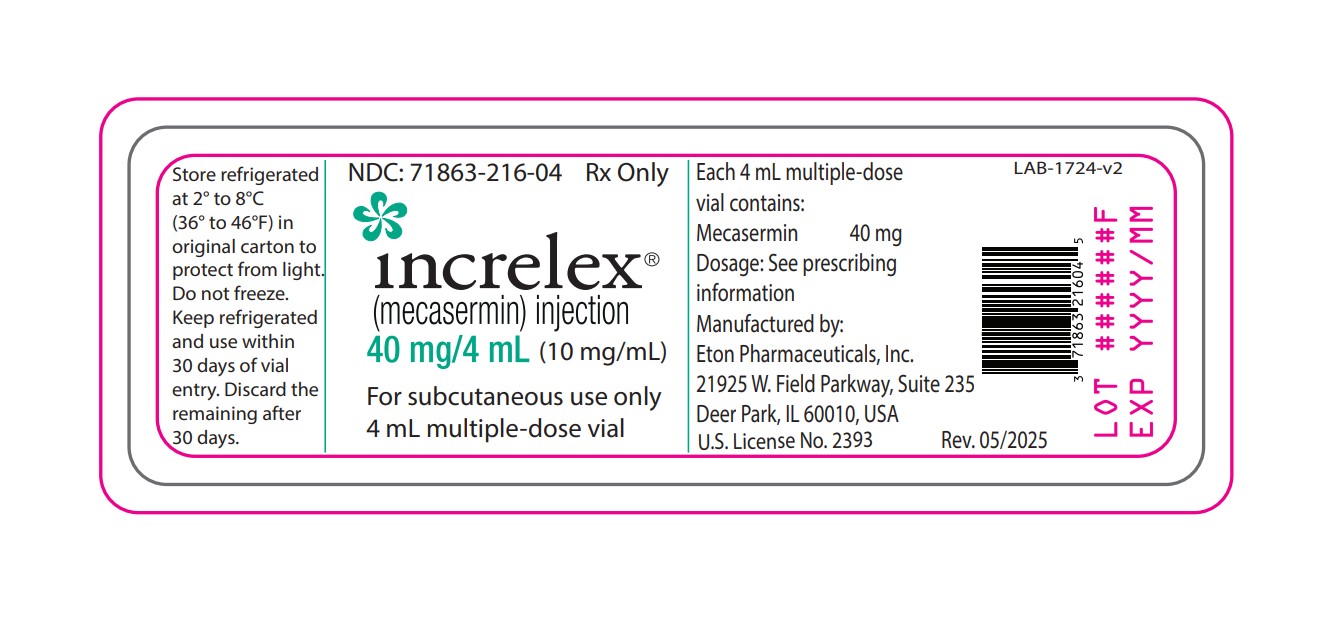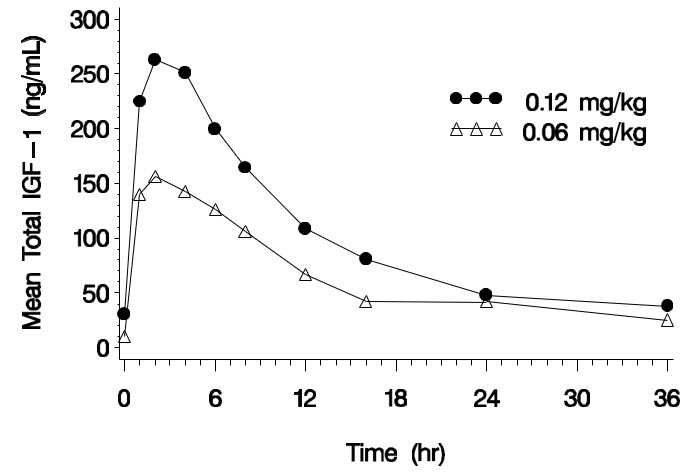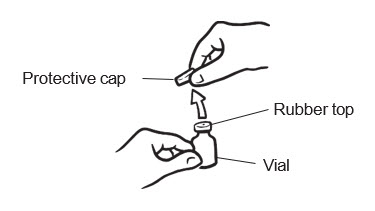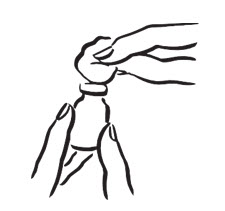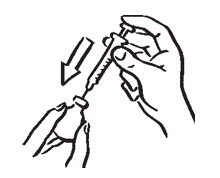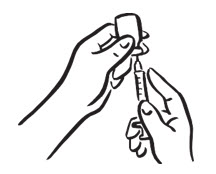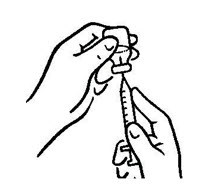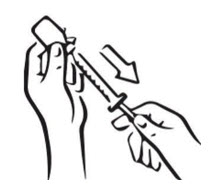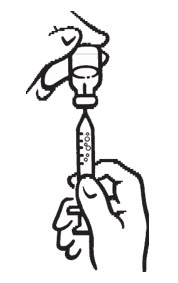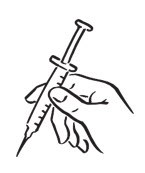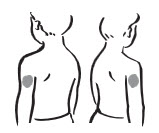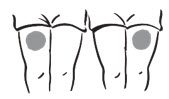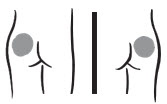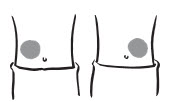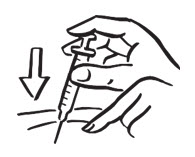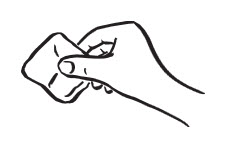 DRUG LABEL: Increlex
NDC: 71863-216 | Form: INJECTION
Manufacturer: Eton Pharmaceuticals, Inc.
Category: prescription | Type: HUMAN PRESCRIPTION DRUG LABEL
Date: 20251001

ACTIVE INGREDIENTS: MECASERMIN 40 mg/4 mL
INACTIVE INGREDIENTS: BENZYL ALCOHOL 36 mg/4 mL; SODIUM CHLORIDE; POLYSORBATE 20; SODIUM ACETATE; ACETIC ACID; WATER

HIGHLIGHTS OF PRESCRIBING INFORMATION

These highlights do not include all the information needed to use INCRELEX®safely and effectively. See full prescribing information for INCRELEX®.
INCRELEX®(mecasermin) injection, for subcutaneous use
Initial U.S. Approval: 2005

RECENT MAJOR CHANGES

Warning and Precautions, Slipped Capital Femoral Epiphysis (5.5) | 05/2025

1 INDICATIONS AND USAGE

INCRELEX (mecasermin) injection is indicated for the treatment of growth failure in pediatric patients 2 years of age and older with severe primary IGF- 1 deficiency or with growth hormone (GH) gene deletion who have developed neutralizing antibodies to GH. (1)

Limitations of use: INCRELEX is not a substitute to GH for approved GH indications.

2 DOSAGE AND ADMINISTRATION

- INCRELEX should be administered subcutaneously. (2.2)
- Injection sites should be rotated to avoid lipohypertrophy. (2.2)
- Recommended starting dosage: 0.04 mg/kg to 0.08 mg/kg twice daily.
  If well-tolerated for at least one week, the dose may be increased by 0.04 mg/kg per dose, to the maximum dose of 0.12 mg/kg given twice daily. (2.1)

3 DOSAGE FORMS AND STRENGTHS

- Injection: 40 mg/4 mL (10 mg/mL) solution supplied in a multiple-dose glass vial (3)

4 CONTRAINDICATIONS

- Known Hypersensitivity to mecasermin (4)
- Closed Epiphyses (4)
- Malignant Neoplasia (4)

5 WARNINGS AND PRECAUTIONS

- Hypoglycemia: Severe hypoglycemia leading to hypoglycemic seizures has been observed with INCRELEX treatment. Administer INCRELEX shortly before or after a meal or snack, because it has insulin-like hypoglycemic effects. (5.1)
- Hypersensitivity and Allergic Reactions, including Anaphylaxis: A low number of cases indicative of anaphylaxis requiring hospitalization have been reported. Parents and patients should be informed that such reactions are possible and that if a systemic allergic reaction occurs, treatment should be interrupted and prompt medical attention should be sought. (5.2)
- Intracranial Hypertension :Funduscopic examination is recommended at the initiation and periodically during the course of INCRELEX therapy. (5.3)
- Lymphoid Tissue Hypertrophy (tonsillar/adenoidal hypertrophy): Patients should have periodic examinations to rule out potential complications and receive appropriate treatment if necessary. (5.4)
- Slipped Capital Femoral Epiphysis (SCFE): Evaluate any child with onset of a limp or hip/knee pain for possible SCFE and osteonecrosis. (5.5)
- Progression of Scoliosis: Monitor any child with scoliosis for progression of the spine curve. (5.6)
- Malignant Neoplasia: Several cases of malignant neoplasia have been observed in pediatric patients treated with INCRELEX. Therapy should be discontinued if evidence of malignant neoplasia develops and appropriate expert medical care sought. (5.7)
- Risk of Serious Adverse Reactions in Infants due to Benzyl Alcohol Preserved Solution: Benzyl alcohol, a preservative in INCRELEX, has been associated with serious adverse reactions, including death, in neonates and infants. Use of INCRELEX in infants is not recommended. (5.8)

6 ADVERSE REACTIONS

Common INCRELEX-related adverse reactions in clinical trials include: hypoglycemia, local and systemic hypersensitivity, tonsillar hypertrophy (6.1).

To report SUSPECTED ADVERSE REACTIONS, contact Eton Pharmaceuticals, Inc. at 1-855-224-0233 or FDA at 1-800-FDA-1088 or www.fda.gov/medwatch.

8 USE IN SPECIFIC POPULATIONS

- Pediatric Use: Safety and effectiveness has not been established in children less than 2 years of age. (8.4)

FULL PRESCRIBING INFORMATION

1 INDICATIONS AND USAGE

Severe Primary IGF-1 Deficiency (Primary IGFD)

INCRELEX is indicated for the treatment of growth failure in pediatric patients 2 years of age and older with:

- severe primary IGF-1 deficiency or
- growth hormone (GH) gene deletion who have developed neutralizing antibodies to GH. Severe Primary IGF-1 deficiency (IGFD) is defined by:
- height standard deviation score ≤ –3.0 and
- basal IGF-1 standard deviation score ≤ –3.0 and
- normal or elevated growth hormone (GH).

Limitations of use:

INCRELEX is not a substitute to GH for approved GH indications.

INCRELEX is not indicated for use in patients with secondary forms of IGF-1 deficiency, such as GH deficiency, malnutrition, hypothyroidism, or chronic treatment with pharmacologic doses of anti-inflammatory corticosteroids.

2 DOSAGE AND ADMINISTRATION

2.1 Recommended Dosage

- Treatment with INCRELEX should be supervised by a physician who is experienced in the diagnosis and management of pediatric patients with short stature associated with severe primary IGF-1 deficiency or with growth hormone gene deletion and who have developed neutralizing antibodies to growth hormone.
- The dosage of INCRELEX should be individualized for each patient. The recommended starting dose of INCRELEX is 0.04 mg/kg to 0.08 mg/kg of body weight twice daily by subcutaneous injection. If well-tolerated for at least one week, the dose may be increased by 0.04 mg/kg of body weight per dose, to the maximum dose of 0.12 mg/kg of body weight given twice daily [see Warnings and Precautions (5.1and 5.7)].
- Preprandial glucose monitoring is recommended at treatment initiation and until a well-tolerated dose is established. If frequent symptoms of hypoglycemia or severe hypoglycemia occur, preprandial glucose monitoring should continue, and glucose monitoring should also occur at the time of event if possible. If hypoglycemia occurs with recommended doses despite adequate food intake, the dose should be reduced. INCRELEX should be administered shortly before or after (± 20 minutes) a meal or snack. If the patient is unable to eat shortly before or after a dose for any reason, that dose of INCRELEX should be withheld.
- If one or more doses of INCRELEX is missed, do not increase the subsequent doses to make up for omitted doses.

2.2 Administration Instructions

INCRELEX is administered by subcutaneous injection only. Do not administer intravenously.

INCRELEX injection sites should be rotated to a different site (upper arm, thigh, buttock or abdomen) with each injection to help prevent lipohypertrophy.

INCRELEX should be administered using sterile disposable syringes and needles. The syringes should be of small enough volume so that the prescribed dose can be withdrawn from the vial with accuracy.

Parenteral drug products should be inspected visually for particulate matter and discoloration prior to administration, whenever solution and container permit. Do not use if the solution is cloudy or contains particulate matter.

If using syringes that measure dose in units, doses in mg/kg must be converted to units using the following formula: Weight (kg) × Dose (mg/kg) × 1 mL/10 mg × 100 units/1 mL = units/injection.

3 DOSAGE FORMS AND STRENGTHS

Injection: 40 mg/4 mL (10 mg/mL) clear and colorless solution in a multiple-dose glass vial.

4 CONTRAINDICATIONS

- Known Hypersensitivity

INCRELEX should not be used by patients who are allergic to mecasermin (rhIGF-1) or any of the inactive ingredients in INCRELEX, or who have experienced a severe hypersensitivity to INCRELEX [see Warnings and Precautions (5.2)and Adverse Reactions (6)].

- Closed Epiphyses

INCRELEX should not be used for growth promotion in patients with closed epiphyses.

- Malignant Neoplasia

INCRELEX is contraindicated in pediatric patients with malignant neoplasia or a history of malignancy [see Warnings and Precautions (5.7)and Adverse Reactions (6)].

5 WARNINGS AND PRECAUTIONS

5.1 Hypoglycemia

Severe hypoglycemia leading to hypoglycemic seizures has been observed with INCRELEX treatment [see Adverse Reactions (6.1)]. Because INCRELEX has insulin-like hypoglycemic effects it should be administered shortly before or after (± 20 minutes) a meal or snack. Glucose monitoring and INCRELEX dose titration are recommended until a well-tolerated dose is established [see Dosage and Administration (2.1)] and subsequently as medically indicated. Special attention should be paid to small children because their oral intake may not be consistent. Patients should avoid engaging in any high- risk activities (e.g., driving, exercise, etc.) within 2 to 3 hours after dosing, particularly during the initiation of INCRELEX treatment until tolerability and a stable dose have been established [see Adverse Reactions (6.1)] . INCRELEX should not be administered when the meal or snack is omitted. The dose of INCRELEX should never be increased to make up for one or more omitted doses.

5.2 Hypersensitivity and Allergic Reactions, including Anaphylaxis

Allergic reactions to INCRELEX have been reported post-marketing. They range from localized (injection site) reactions to systemic reactions, including anaphylaxis requiring hospitalization. Parents and patients should be informed that such reactions are possible and that if a systemic allergic reaction occurs, treatment should be interrupted and prompt medical attention should be sought. [see Contraindications (4)and Adverse Reactions (6)]

5.3 Intracranial Hypertension

Intracranial hypertension (IH) with papilledema, visual changes, headache, nausea and/or vomiting have occurred in patients treated with INCRELEX. IH-associated signs and symptoms resolved after interruption of dosing. Funduscopic examination is recommended at the initiation and periodically during the course of INCRELEX therapy. [see Adverse Reactions (6)].

5.4 Lymphoid Tissue Hypertrophy

Lymphoid tissue (e.g., tonsillar and adenoidal) hypertrophy associated with complications, such as snoring, sleep apnea, and chronic middle-ear effusions have been reported with the use of INCRELEX. Patients should have periodic examinations to rule out such potential complications and receive appropriate treatment if necessary [see Adverse Reactions (6)].

5.5 Slipped Capital Femoral Epiphysis

Slipped capital femoral epiphysis can occur in patients who experience rapid growth. Slipped capital femoral epiphysis may lead to osteonecrosis. Cases of slipped capital femoral epiphysis with or without osteonecrosis have been reported in pediatric patients receiving products indicated to treat growth failure and/or short stature, including INCRELEX. Any pediatric patient with the onset of a limp or complaints of hip or knee pain during INCRELEX therapy should be evaluated for slipped capital femoral epiphysis and osteonecrosis and managed accordingly.

5.6 Progression of Preexisting Scoliosis

Progression of scoliosis may occur in patients who experience rapid growth. Because INCRELEX increases growth rate, patients with a history of scoliosis who are treated with INCRELEX should be monitored for progression of scoliosis.

5.7 Malignant Neoplasia

There have been postmarketing reports of malignant neoplasms in pediatric patients who have received treatment with INCRELEX [see Adverse Reactions (6)] . The cases of malignant neoplasms represented a variety of different malignancies. It is unknown whether there is any relationship between INCRELEX therapy and new occurrence of neoplasia. The occurrence of neoplasia was mostly reported in patients with rare genetic conditions of short stature associated with an increased risk of cancer, or in patients with other cancer predisposing conditions. The tumors were observed also more frequently in patients who received INCRELEX at higher than recommended doses, or at doses that produced serum IGF-1 levels above the normal reference ranges for age and sex. Monitor all patients receiving INCRELEX carefully for development of neoplasms. Advise patients/caregivers to report development of new neoplasms. If malignant neoplasia develops, discontinue INCRELEX treatment [see Contraindications (4)] .

5.8 Risk of Serious Adverse Reactions in Infants due to Benzyl Alcohol Preserved Solution

Serious and fatal adverse reactions including "gasping syndrome" can occur in neonates and infants treated with benzyl alcohol-preserved drugs, including INCRELEX. The "gasping syndrome" is characterized by central nervous system depression, metabolic acidosis, and gasping respirations.

Use of INCRELEX in infants is not recommended [see Use in Specific Populations 8.4)] .

6 ADVERSE REACTIONS

The following serious adverse reactions are described below and elsewhere in the labeling:

- Hypoglycemia [see Warnings and Precautions (5.1)].
- Hypersensitivity and Allergic Reactions, including Anaphylaxis [see Warnings and Precautions (5.2)]
- Intracranial hypertension (IH) [see Warnings and Precautions (5.3)]
- Tonsillar and Adenoidal Hypertrophy and related complications [see Warnings and Precautions (5.4)]
- Slipped Capital Femoral Epiphysis [see Warnings and Precautions (5.5)]
- Progression of Preexisting Scoliosis [see Warnings and Precautions (5.6)]
- Malignant Neoplasia [see Warnings and Precautions (5.7)]
- Benzyl Alcohol [see Warnings and Precautions (5.8)]

6.1 Clinical Trials Experience

Because clinical trials are conducted under widely varying conditions, adverse reaction rates observed in the clinical trials of a drug cannot be directly compared to rates in the clinical trials of another drug and may not reflect the rates observed in practice.

In clinical studies of 71 subjects with Primary IGFD treated for a mean duration of 3.9 years and representing 274 subject-years, no subjects withdrew from any clinical study because of adverse reactions. Adverse reactions to INCRELEX treatment that occurred in 5% or more of these study participants are listed below by organ class.

- Metabolism and Nutrition Disorders:hypoglycemia
- General Disorders and Administrative Site Conditions:lipohypertrophy, bruising
- Infections and Infestations:otitis media, serous otitis media
- Respiratory, Thoracic and Mediastinal Disorders:snoring, tonsillar hypertrophy
- Nervous System Disorders:headache, dizziness, convulsions
- Gastrointestinal Disorders:vomiting
- Ear and Labyrinth Disorders:hypoacusis, fluid in middle ear, ear pain, abnormal tympanometry
- Investigations:cardiac murmur
- Musculoskeletal and Connective Tissue Disorders:arthralgia, pain in extremity
- Blood and Lymphatic System Disorders:thymus hypertrophy
- Surgical and Medical Procedures:ear tube insertion

Hypoglycemia was reported by 30 subjects (42%) at least once during their course of therapy. Most cases of hypoglycemia were mild or moderate in severity. Five subjects had severe hypoglycemia (requiring assistance and treatment) on one or more occasions and 4 subjects experienced hypoglycemic seizures/loss of consciousness on one or more occasions. Of the 30 subjects reporting hypoglycemia, 14 (47%) had a history of hypoglycemia prior to treatment. The frequency of hypoglycemia was highest in the first month of treatment, and episodes were more frequent in younger children. Symptomatic hypoglycemia was generally avoided when a meal or snack was consumed either shortly (i.e., 20 minutes) before or after the administration of INCRELEX.

Tonsillar hypertrophy was noted in 11 (15%) subjects in the first 1 to 2 years of therapy with lesser tonsillar growth in subsequent years. Tonsillectomy or tonsillectomy/adenoidectomy was performed in 7 subjects; 3 of these had obstructive sleep apnea, which resolved after the procedure in all three cases.

Intracranial hypertension occurred in three subjects. In two subjects the events resolved without interruption of INCRELEX treatment. INCRELEX treatment was discontinued in the third subject and resumed later at a lower dose without recurrence.

Mild elevations in the serum AST and LDH were found in a significant proportion of patients before and during treatment. Rise in levels of these serum enzymes did not lead to treatment discontinuation. ALT elevations were occasionally noted during treatment.

Renal and splenic lengths (measured by ultrasound) increased rapidly on INCRELEX treatment during the first years of therapy. This lengthening slowed down subsequently; though in some patients, renal and/or splenic length reached or surpassed the 95thpercentile. Renal function (as defined by serum creatinine and calculated creatinine clearance) was normal in all patients, irrespective of renal growth.

Elevations in cholesterol and triglycerides to above the upper limit of normal were observed before and during treatment.

Echocardiographic evidence of cardiomegaly/valvulopathy was observed in a few individuals without associated clinical symptoms. The relation of these cardiac changes to drug treatment cannot be assessed due to underlying disease and the lack of a control group.

Thickening of the soft tissues of the face was observed in several patients and should be monitored during INCRELEX treatment.

6.2 Postmarketing Experience

The following adverse reactions have been identified during post approval use of INCRELEX. Because these reactions are reported voluntarily from a population of uncertain size, it is not always possible to reliably estimate their frequency or establish a causal relationship to drug exposure.

Systemic hypersensitivity: anaphylaxis, generalized urticaria, angioedema, dyspnea

In the post-marketing setting, the frequency of cases indicative of anaphylaxis was estimated to be 0.3%. Symptoms included hives, angioedema, and dyspnea, and some patients required hospitalization. Upon re-administration, symptoms did not re-occur in all patients.

Local allergic reactions at the injection site: pruritus, urticaria

Skin and Subcutaneous Tissue Disorders: alopecia, hair texture abnormal

General Disorders and Administrative Site Conditions: injection site reactions (e.g. erythema, pain, hematoma, hemorrhage, induration, rash, swelling)

Musculoskeletal and Connective Tissue Disorders: osteonecrosis/avascular necrosis (occasionally associated with slipped capital femoral epiphysis)

Neoplasms Benign, Malignant and Unspecified (including cysts and polyps)

8 USE IN SPECIFIC POPULATIONS

8.1 Pregnancy

Risk Summary

There are no available data on INCRELEX use in pregnant women. Exposure to INCRELEX during pregnancy is unlikely because the drug is not indicated for use after epiphyseal closure. In animal reproduction studies, there were no observed embryo-fetal development abnormalities with intravenous administration of INCRELEX to pregnant rats and rabbits during fetal organogenesis given at exposures up to 11 and 3 times the maximum recommended human dose (MRHD) of 0.24 mg/kg/day based on body surface area (BSA), respectively (see Data) .

The estimated background risk of birth defects and miscarriage for the indicated population is unknown. In the U.S. general population, the estimated background risk of major birth defects and miscarriage in clinically recognized pregnancies is 2-4% and 15-20%, respectively.

Data

Animal Data

Studies to assess embryo-fetal toxicity evaluated the effects of INCRELEX during organogenesis in Sprague Dawley rats given 1, 4, and 16 mg/kg/day and in New Zealand White rabbits given 0.125, 0.5, and 2 mg/kg/day, administered intravenously. There were no observed embryo-fetal developmental abnormalities in rats given up to 16 mg/kg/day (11 times the MRHD based on BSA comparison). In the rabbit study, the NOAEL for fetal toxicity was 0.5 mg/kg/day (approximately equivalent to the MRHD based on BSA) due to an increase in fetal death at 2 mg/kg. INCRELEX displayed no teratogenicity or maternal toxicity in rabbits given up to 2 mg/kg (3 times the MRHD based on BSA).

8.2 Lactation

Risk Summary

There is no information available on the presence of mecasermin in human or animal milk, the effects of the drug on the breastfed infant, or the effects of the drug on milk production. The developmental and health benefits of breastfeeding should be considered along with the mother's clinical need for INCRELEX and any potential adverse effects on the breast-fed child from INCRELEX or from the underlying maternal condition.

8.4 Pediatric Use

Toxicity (Gasping Syndrome) with Benzyl Alcohol

Serious adverse reactions including fatal reactions and the "gasping syndrome" occurred in premature neonates and infants in the intensive care unit who received drugs containing benzyl alcohol as a preservative. In these cases, benzyl alcohol dosages of 99 mg/kg/day to 234 mg/kg/day produced high levels of benzyl alcohol and its metabolites in the blood and urine (blood levels of benzyl alcohol were 0.61 mmol/L to 1.378 mmol/L). INCRELEX contains 9 mg/mL benzyl alcohol as a preservative.

Additional adverse reactions included gradual neurological deterioration, seizures, intracranial hemorrhage, hematologic abnormalities, skin breakdown, hepatic and renal failure, hypotension, bradycardia, and cardiovascular collapse. Preterm, low-birth weight infants may be more likely to develop these reactions because they may be less able to metabolize benzyl alcohol. Use of INCRELEX in infants is not recommended [see Warnings and Precautions (5.8)] .

Safety and effectiveness in pediatric patients below the age of 2 years of age have not been established.

8.5 Geriatric Use

The safety and effectiveness of INCRELEX in patients aged 65 and over has not been established.

10 OVERDOSAGE

Treatment of acute overdose should be directed at reversing hypoglycemia. Oral glucose or food should be consumed. If the overdose results in loss of consciousness, intravenous glucose or parenteral glucagon may be required to reverse the hypoglycemic effects.

A small number of overdose cases have been reported in the post-marketing experience. In one case of acute overdose, a 3-year old patient experienced hypoglycemia after receiving one 4 mg dose of INCRELEX (a 10-fold increase beyond the prescribed dose). The event resolved following treatment with IV glucose.

Long term overdosage with INCRELEX may result in signs and symptoms of acromegaly.

11 DESCRIPTION

Mecasermin is a human insulin-like growth factor-1 (rhIGF-1) produced by recombinant DNA technology. IGF-1 consists of 70 amino acids in a single chain with three intramolecular disulfide bridges and a molecular weight of 7649 Da. The amino acid sequence of the product is identical to that of endogenous human IGF-1. The rhIGF-1 protein is synthesized in bacteria (E. coli) that have been modified by the addition of the gene for human IGF-1.

INCRELEX (mecasermin) injection is a sterile, aqueous, clear and colorless solution intended for subcutaneous injection. Each multiple-dose vial of INCRELEX contains 40 mg of mecasermin in 4 mL solution, and each mL contains 10 mg mecasermin, 9 mg benzyl alcohol, 0.43 mg glacial acetic acid, 2 mg polysorbate 20, 3.51 mg sodium acetate, and 5.84 mg sodium chloride in Water for Injection, USP at a pH of approximately 5.4.

12 CLINICAL PHARMACOLOGY

12.1 Mechanism of Action

Insulin-like growth factor-1 (IGF-1) is a key hormonal mediator on statural growth. Under normal circumstances, growth hormone (GH) binds to its receptor in the liver, and other tissues, and stimulates the synthesis/secretion of IGF-1. In target tissues, the Type 1 IGF-1 receptor, which is homologous to the insulin receptor, is activated by IGF-1, leading to intracellular signaling which stimulates multiple processes resulting in statural growth. The metabolic actions of IGF-1 are in part directed at stimulating the uptake of glucose, fatty acids, and amino acids so that metabolism supports growing tissues.

12.2 Pharmacodynamics

The following actions have been demonstrated for endogenous human IGF-1:

Tissue Growth– 1) Skeletal growth occurs at the cartilage growth plates of the epiphyses of bones where stem cells divide to produce new cartilage cells or chondrocytes. The growth of chondrocytes is under the control of IGF-1 and GH. The chondrocytes become calcified so that new bone is formed allowing the length of the bones to increase. This results in skeletal growth until the cartilage growth plates fuse at the end of puberty. 2) Cell growth: IGF-1 receptors are present on most types of cells and tissues. IGF-1 has mitogenic activities that lead to an increased number of cells in the body. 3) Organ growth: Treatment of IGF-1 deficient rats with rhIGF-1 results in whole body and organ growth.

Carbohydrate Metabolism–IGF-1 suppresses hepatic glucose production and stimulates peripheral glucose utilization and therefore has a hypoglycemic potential. IGF-1 has inhibitory effects on insulin secretion.

12.3 Pharmacokinetics

Absorption– The absolute bioavailability of rhIGF-1 after subcutaneous administration in healthy subjects is estimated to be close to 100%. However, the absolute bioavailability of INCRELEX given subcutaneously to subjects with primary insulin-like growth factor-1 deficiency (Primary IGFD) has not been determined.

Distribution– In blood, IGF-1 is bound to six IGF binding proteins, with > 80% bound as a complex with IGFBP-3 and an acid-labile subunit. IGFBP-3 is greatly reduced in subjects with severe Primary IGFD, resulting in increased clearance of IGF-1 in these subjects relative to healthy subjects. The total IGF-1 volume of distribution after subcutaneous administration in subjects with severe Primary IGFD is estimated to be 0.257 (± 0.073) L/kg at an INCRELEX dose of 0.045 mg/kg and is estimated to increase as the dose of INCRELEX increases.

Elimination– IGF-1 is metabolized by both liver and kidney. The mean terminal t1/2 after single subcutaneous administration of 0.12 mg/kg INCRELEX in pediatric subjects with severe Primary IGFD is estimated to be 5.8 hours. Clearance of INCRELEX is inversely proportional to IGF binding protein- 3 (IGFBP-3) levels. CL/F is estimated to be 0.04 L/hr/kg at 0.5 micrograms/mL of IGFBP-3, and 0.01 L/hr/kg at 3 micrograms/mL IGFBP-3; the latter is the median IGFBP-3 in subjects with normal IGF-1 serum levels.

Gender– In children with Primary IGFD there were no apparent differences between males and females in the pharmacokinetics of INCRELEX.

Race–The effect of race on pharmacokinetics of INCRELEX has not been studied.

Table 1. Summary of INCRELEX Single-Dose Pharmacokinetic Parameters in Children with Severe Primary IGFD (0.12 mg/kg, SC)
 | Cmax (ng/mL) | Tmax (hr) | AUC0-8 (hr*ng/mL) | t1/2 (hr) | Vd/F (L/kg) | CL/F (L/hr/kg)
n | 3 | 3 | 3 | 3 | 12 [Data represents 3 subjects each at doses 0.015, 0.03, 0.06, and 0.12 mg/kg SC.] | 12
Mean | 234 | 2 | 2932 | 5.8 | 0.257 | 0.0424
CV% | 23 | 0 | 50 | 64 | 28 | 38
Cmax= maximum concentration; Tmax= time of maximum concentration; AUC0-8= area under the curve; t1/2= half-life; Vd/F = apparent volume of distribution; CL/F = apparent systemic clearance; SC = subcutaneous injection; CV% = coefficient of variation in %.
Male/female data combined, ages 12 to 22 years.
PK parameters based on baseline adjusted plasma concentrations.

Figure 1. Mean Total IGF-1 Concentration after a Single Subcutaneous Dose of INCRELEX in Children with Severe Primary IGFD (0.06 mg/kg and 0.12 mg/kg, n=3 per group)

Renal impairment– No studies have been conducted in Primary IGFD children with renal impairment.

Hepatic impairment– No studies have been conducted to determine the effect of hepatic impairment on the pharmacokinetics of rhIGF-1 in Primary IGFD children with hepatic impairment.

12.6 Immunogenicity

The observed incidence of anti-drug antibodies is highly dependent on the sensitivity and specificity of the assay. Differences in assay methods preclude meaningful comparisons of the incidence of anti-drug antibodies in the studies described below with the incidence of anti-drug antibodies in other studies, including those of INCRELEX or other growth hormones.

Anti-IGF-1 antibodies were present at one or more of the periodic assessments in 14 of 23 children with Primary IGFD treated for 2 years. However, no clinical consequences of these antibodies were observed (e.g., attenuation of growth).

13 NONCLINICAL TOXICOLOGY

13.1 Carcinogenesis, Mutagenesis, Impairment of Fertility

Carcinogenesis: INCRELEX was tumorigenic in rats in a study using doses of 0, 0.25, 1, 4, and 10 mg/kg/day by subcutaneous injection for up to 2 years. The incidence of adrenal medullary hyperplasia and pheochromocytoma increased in male rats given ≥1 mg/kg/day (below clinical exposure at the maximum recommended human dose [MRHD] based on AUC) and in female rats at all dose levels (below clinical exposure at the MRHD based on AUC). The incidence of keratoacanthoma in the skin increased in male rats given 4 and 10 mg/kg/day (approximately the clinical exposure at the MRHD based on AUC). The incidence of mammary gland carcinoma in male rats increased in animals treated with 10 mg/kg/day (3 times the MRHD based on AUC). Only doses that exceeded the maximum tolerated dose (MTD) (based on excess mortality secondary to IGF-1 induced hypoglycemia) caused skin and mammary tumors.

Mutagenesis: INCRELEX was not clastogenic in the in vitro chromosome aberration assay and the in vivo mouse micronucleus assay.

Impairment of fertility: INCRELEX had no effects on fertility in rats using intravenous doses 0.25, 1, and 4 mg/kg/day (up to 3 times the clinical exposure at the MRHD based on BSA).

14 CLINICAL STUDIES

14.1 Effects of INCRELEX Treatment in Children with Severe Primary Insulin-like Growth Factor-1 Deficiency (Severe Primary IGFD)

Five clinical studies (four open-label and one double-blind, placebo-controlled), with subcutaneous doses of INCRELEX generally ranging from 0.06 to 0.12 mg/kg (60 to 120 micrograms/kg) administered twice daily, were conducted in 71 pediatric subjects with severe Primary IGFD. Patients were enrolled in the trials on the basis of extreme short stature, slow growth rates, low IGF-1 serum concentrations, and normal growth hormone secretion. Data from these 5 clinical studies were pooled for a global efficacy and safety analysis. Baseline characteristics for the patients evaluated in the primary and secondary efficacy analyses were (mean, SD): chronological age (years): 6.7 ± 3.8; height (cm): 84.8 ± 15.3 cm; height standard deviation score (SDS): -6.7 ± 1.8; height velocity (cm/yr): 2.8 ± 1.8; height velocity SDS: -3.3 ± 1.7; IGF-1 (ng/mL): 21.6 ± 20.6; IGF-1 SDS: -4.3 ± 1.6; and bone age (years): 4.2 ± 2.8. Sixty-one subjects had at least one year of treatment. Fifty-three (87%) had Laron Syndrome; 7 (11%) had GH gene deletion, and 1 (2%) had neutralizing antibodies to GH. Thirty-seven (61%) of the subjects were male; forty-eight (79%) were Caucasian. Fifty-six (92%) of the subjects were pre-pubertal at baseline.

Annual results for height velocity, height velocity SDS, and height SDS are shown in Table 2. Pre- treatment height velocity data were available for 58 subjects. The height velocities at a given year of treatment were compared by paired t-tests to the pre-treatment height velocities of the same subjects completing that treatment year.

Table 2: Annual Height Results by Number of Years Treated with INCRELEX
 | Pre-Tx | Year 1 | Year 2 | Year 3 | Year 4 | Year 5 | Year 6 | Year 7 | Year 8
Height Velocity (cm/yr)
N | 58 | 58 | 48 | 38 | 23 | 21 | 20 | 16 | 13
Mean (SD) | 2.8 (1.8) | 8.0 (2.2) | 5.8 (1.5) | 5.5 (1.8) | 4.7 (1.6) | 4.7 (1.6) | 4.8 (1.5) | 4.6 (1.5) | 4.3 (1.1)
Mean (SD) for change from pre-treatment |  | +5.2 (2.6) | +2.9 (2.4) | +2.3 (2.4) | +1.5 (2.2) | +1.5 (1.8) | +1.5 (1.7) | +1.0 (2.1) | +0.7 (2.5)
P-value for change from pre-treatment [P-values for comparison versus pre-treatment values are computed using paired t-tests.] |  | <0.0001 | <0.0001 | <0.0001 | 0.0045 | 0.0015 | 0.0009 | 0.0897 | 0.3059
Height Velocity SDS
N | 58 | 58 | 47 | 37 | 22 | 19 | 18 | 15 | 11
Mean (SD) | -3.3 (1.7) | 1.9 (3.0) | -0.2 (1.6) | -0.2 (2.0) | -0.7 (2.1) | -0.6 (2.1) | -0.4 (1.4) | -0.4 (1.9) | -0.4 (1.9)
Mean (SD) for change from pre-treatment |  | +5.2 (3.1) | +3.1 (2.3) | +2.9 (2.3) | +2.2 (2.2) | +2.5 (2.2) | +2.7 (1.7) | +2.5 (2.1) | +2.7 (2.8)
Height SDS
N | 61 | 61 | 51 | 40 | 24 | 21 | 20 | 16 | 13
Mean (SD) | -6.7 (1.8) | -5.9 (1.8) | -5.6 (1.8) | -5.4 (1.8) | -5.5 (1.9) | -5.6 (1.8) | -5.4 (1.8) | -5.2 (2.0) | -5.2 (2.0)
Mean (SD) for change from pre-treatment |  | +0.8 (0.5) | +1.2 (0.8) | +1.4 (1.1) | +1.3 (1.2) | +1.4 (1.3) | +1.4 (1.2) | +1.4 (1.1) | +1.5 (1.1)
Pre-Tx = Pre-treatment; SD = Standard Deviation; SDS = Standard Deviation Score

Forty-nine subjects were included in an analysis of the effects of INCRELEX on bone age advancement. The mean ± SD change in chronological age was 4.9 ± 3.4 years and the mean ± SD change in bone age was 5.3 ± 3.4 years.

16 HOW SUPPLIED/STORAGE AND HANDLING

How Supplied

INCRELEX injection is supplied as a 40 mg/4 mL (10 mg/mL) sterile, clear, and colorless solution in multiple-dose glass vials (NDC-71863-216-04).

Storage and Handling

Before Opening– Vials of INCRELEX are stable when refrigerated at 2° to 8°C (36° to 46°F). Avoid freezing the vials of INCRELEX. Protect from direct light. Expiration dates are stated on the labels.

After Opening– Vials of INCRELEX are stable for 30 days after initial vial entry when stored refrigerated at 2° to 8°C (36° to 46°F). Avoid freezing the vials of INCRELEX. Protect from direct light.

INCRELEX should not be used after its expiration date. Keep refrigerated and use within 30 days of initial vial entry. Remaining unused material should be discarded.

17 PATIENT COUNSELING INFORMATION

Advise patients and/or caregivers to read the FDA-approved patient labeling (Patient Information) and Instructions for Use.

Counsel patients and/or parents that there have been occurrences of malignant neoplasia observed among pediatric patients who received treatment with INCRELEX. Instruct patients and/or parents to monitor for development of any new growth or symptoms of cancer and to report it immediately.

Instruct patients and/or caregivers in the proper administration of INCRELEX. Give INCRELEX shortly before or after (20 minutes on either side of) a meal or snack. Do not give INCRELEX when the meal or snack is omitted. Do not increase the dose of INCRELEX to make up for one or more omitted doses. INCRELEX therapy will be initiated at a low dose and the dose should be increased only if no hypoglycemia episodes have occurred after at least 7 days of dosing. Educate patients and caregivers on how to recognize the signs and symptoms of hypoglycemia.

Educate patients and caregivers on the identification of signs and symptoms of serious allergic reactions to INCRELEX and the need to seek prompt medical contact should such a reaction occur. Instruct patients and caregivers to discontinue INCRELEX if a reaction occurs.

Manufactured by:
Eton Pharmaceuticals, Inc.
21925 W Field Pkwy Ste 235,
Deer Park, IL 60010
U.S. License No. 2393

At:
Simtra Deutschland GmbH
Kantstrasse 2, 33790
Halle (Westfalen), Germany

PL-24-2.0

PATIENT INFORMATION
INCRELEX®(EENK-RUH-LEX)
(mecasermin) injection for subcutaneous use

Read the Patient Information that comes with INCRELEX before your child starts receiving INCRELEX and each time your child gets a refill. There may be new information. This Patient Information leaflet does not take the place of talking with your child's doctor about your child's medical condition or treatment.

What is INCRELEX?

- INCRELEX is a liquid that contains man-made insulin-like growth factor-1 (IGF-1). INCRELEX is used to treat children who are very short for their age because their bodies do not make enough IGF-1. This condition is called primary IGF-1 deficiency.
- IGF-1 should not be used instead of growth hormone.
- It is not known if INCRELEX is safe and effective in children under 2 years of age.

Who should not receive INCRELEX?
Your child should not receive INCRELEX if your child:

- is allergic to mecasermin or any of the ingredients in INCRELEX. See the end of this Patient Information leaflet for a complete list of ingredients in INCRELEX. Check with your child's doctor if you are not sure.
- has finished growing (the bone growth plates are closed).
- has any cancerous tumors or growths; or has a history of cancer or a condition that increases the risk of cancer.

Your child should never receive INCRELEX through a vein.

What should I tell my child's doctor before my child starts receiving INCRELEX?
Tell your child's doctor about all of your child's medical conditions, including if your child:

- has diabetes.
- has a curved spine (scoliosis).
- is pregnant or you think your child might be pregnant. It is not known if INCRELEX can harm an unborn baby.
- is breastfeeding or plans to breastfeed. Talk to your child's doctor about the best way for your child to feed her baby if she receives INCRELEX.

Tell your child's doctor about all the medicines your child takes, including prescription and over-the-counter medicines, vitamins, and herbal supplements. Especially tell your child's doctor if your child takes insulin or other anti-diabetes medicines. A change in dose may be needed for these medicines.

How should my child receive INCRELEX?

- Use INCRELEX exactly as prescribed for your child. Your child's doctor or nurse should teach you how to inject INCRELEX. Do not give your child INCRELEX unless you understand all of the instructions.
- See the " Instructions for Use" at the end of this Patient Information leaflet.
- Inject INCRELEX under your child's skin 20 minutes before or 20 minutes after a meal or snack.
- Skip your child's dose of INCRELEX if your child cannot eat for any reason. Do notgive your child an extra dose of INCRELEX or increase the amount of your child's dose to make up for a missed dose.

What are the possible side effects of INCRELEX?
INCRELEX may cause serious side effects, including:

- Low blood sugar (hypoglycemia). INCRELEX may lower blood sugar levels. It is important to only give your child INCRELEX 20 minutes before or 20 minutes after a meal or snack to reduce the chances of low blood sugar. Do not give your child INCRELEX if your child cannot eat. Signs of low blood sugar include:

- dizziness
- tiredness
- restlessness
- hunger
- irritability

- trouble concentrating
- sweating
- nausea
- fast or irregular heartbeat

Severe hypoglycemia may cause unconsciousness, seizures, or death.If your child receives INCRELEX, they should avoid participating in high risk activities (e.g. driving, exercise, etc.) within 2 to 3 hours after the INCRELEX injection, especially at the beginning of INCRELEX treatment.
Before beginning treatment with INCRELEX your child's doctor or nurse will explain to you how to treat hypoglycemia. Your child should always have a source of sugar such as orange juice, glucose gel, candy, or milk available in case symptoms of hypoglycemia happen. For severe hypoglycemia, if your child is not responsive and cannot drink sugar-containing fluids, you should get emergency medical help for your child right away. Your doctor or nurse will show you how to give the injection.

- Allergic reactions. See " Who should not receive INCRELEX?" Allergic reactions are a serious but common side effect of INCRELEX. Your child may have a mild or serious allergic reaction with INCRELEX. Call your child's doctor right away if your child gets a rash or hives. Hives, also known as urticaria, appear as a raised, itchy skin reaction. Hives appear pale in the middle with a red rim around it. Hives generally appear minutes to hours after the injection and may sometimes occur at many places on the skin. Stop taking INCRELEX and get medical help right away if your child has trouble breathing or goes into shock, with symptoms like dizziness, pale, clammy skin or passing out.

INCRELEX can also cause reactions at the injection site including:

- loss of fat (lipoatrophy)
- increase of fat (lipohypertrophy)
- pain, redness, or bruising

Injection site reactions can be avoided by changing (rotating) the injection site at each injection.

- Increased pressure in the brain (intracranial hypertension).INCRELEX, like growth hormone, can sometimes cause a temporary increase in pressure within the brain. The symptoms of intracranial hypertension can include headache, nausea and vomiting. Tell your doctor if your child has a headache with vomiting. Your doctor can then check to see if intracranial hypertension is present. If it is present, your child's doctor may decide to temporarily reduce or stop INCRELEX therapy.
- Enlarged tonsils.Some signs of enlarged tonsils include: snoring, difficulty breathing, sleep apnea (a condition where breathing stops briefly during sleep), or fluid in the middle-ear. Sleep apnea can cause excessive daytime sleepiness. Call your child's doctor if these symptoms bother your child. Your child's doctor should do regular exams to check your child's tonsils.
- A bone problem called slipped capital femoral epiphysis.This happens when the top of the upper leg (femur) slips apart. This may lead to a serious condition where bone tissue dies due to a lack of blood supply (osteonecrosis). Get medical help for your child right away if your child develops a limp or has hip or knee pain.
- Worsened scoliosis(caused by rapid growth) .If your child has scoliosis, your child will need to be checked often for an increase in the curve of the spine.
- Tumor Growths. Several cases of cancerous tumors have been observed in pediatric patients who received treatment with INCRELEX. Tell your doctor immediately if your child develops any new growths or symptoms of cancer.
- Benzyl alcohol toxicity.Benzyl alcohol is a preservative in INCRELEX. Benzyl alcohol can cause serious side effects, including death in infants who have received medicines that contain the benzyl alcohol preservative.

The most common side effects of INCRELEX include: hypoglycemia (low blood sugar), injection site reactions, allergic reactions and enlarged tonsils.
Call your child's doctor if your child has any side effects that bothers them or that does not go away.
These are not all the possible side effects of INCRELEX. For more information, ask your child's doctor or pharmacist.
Call your doctor for medical advice about side effects. You may report side effects to FDA at 1-800-FDA-1088.

How should I store INCRELEX?

- Before Opening: Store new, unopened vials of INCRELEX in the refrigerator between 36°F to 46°F (2°C to 8°C).
- After Opening: Store opened vials of INCRELEX in the refrigerator between 36°F to 46°F (2°C to 8°C) for 30 days after you start using the vial. Throw away any unused INCRELEX after 30 days.
- Do notfreeze INCRELEX. If a vial freezes, throw it away.
- Keep INCRELEX out of direct light.
- Do notuse INCRELEX after the expiration date printed on the label.

Keep INCRELEX and all medicines out of the reach of children.

General information about the safe and effective use of INCRELEX.
Medicines are sometimes prescribed for purposes other than those listed in a Patient Information leaflet. Do not give INCRELEX to your child for a condition for which it was not prescribed. Do not give INCRELEX to a person other than your child. It may harm them.
This Patient Information leaflet summarizes the most important information about INCRELEX. If you would like more information, talk to your child's doctor. You can also ask your child's doctor or pharmacist for information about INCRELEX that is written for health professionals.

What are the ingredients in INCRELEX?
Active ingredient: mecasermin
Inactive ingredients: benzyl alcohol, glacial acetic acid, polysorbate 20, sodium acetate, sodium chloride, and Water for Injection, USP.
Manufactured by: Eton Pharmaceuticals, Inc. 21925 W Field Pkwy Ste 235, Deer Park, IL 60010, USA U.S. License No. 2393
At: Simtra Deutschland GmbH, Kantstrasse 2, 33790 Halle (Westfalen), Germany
INCRELEX is a registered trademark of Eton Pharmaceuticals, Inc.
© 2025. All rights reserved.
For more information go to www.Increlex.com or call 1-855-224-0233.

This Patient Information has been approved by the U.S. Food and Drug Administration.

Revised: 10/2025

PL-22-2.0

INSTRUCTIONS FOR USE

INCRELEX®(EENK-RUH-LEX)
(mecasermin) injection
for subcutaneous use

Read this Instructions for Use before you start using INCRELEX and each time you get a refill. There may be new information. This information does not take the place of talking to your child's doctor about your child's medical condition or treatment.

Do not share your child's needles and syringes with another person.Your child may give another person an infection or your child could get an infection from them.

Important:

- Inject INCRELEX exactly as your child's doctor or nurse has shown you.
- Follow your doctor's instructions for the type of syringe and needle to use to prepare and inject your child's dose of INCRELEX.
- Always use a new, unopened needle and syringe for each injection.
- Only use single-use, disposable needles and syringes. Never reuse disposable needles and syringes.
- Throw away used needles and syringes in a puncture-resistant, disposable sharps container as soon as you finish giving the injection. See step 5 " How should I throw away (dispose of) used needles and syringes?" at the end of these instructions.

Supplies needed to give the injection:

- 1 vial of INCRELEX
- 1 alcohol swab
- 1 gauze or cotton ball
- alcohol (to clean the skin at the injection site)
- 1 sharps container for throwing away (disposing of) used needles and syringes. See step 5 " How should I throw away (dispose of) used needles and syringes?" at the end of these instructions.

Preparing the Dose:

1. Wash your hands before getting INCRELEX ready for your child's injection.
2. Check the liquid to make sure it is clear and colorless. Do notuse if it is cloudy or if you see particles.
3. Check the expiration date printed on the label of the vial. Do notuse INCRELEX if the expiration date has passed.
4. If you are using a new vial, remove the protective cap. Do not remove the rubber top (see Figure 1).
  Figure 1: Remove the protective cap
5. Wipe the rubber top on the vial with an alcohol swab (see Figure 2).
  Figure 2: Wipe rubber top with alcohol swab
6. Before putting the needle into the vial, pull back on plunger to draw air into the syringe equal to the INCRELEX dose. Put the needle through the rubber top of the vial and push the plunger to inject air into the vial (see Figure 3).
  Figure 3: Inject air into vial
7. Leave the syringe in the vial and turn both upside down. Hold the syringe and vial firmly (see Figure 4).
  Figure 4: Prepare to withdraw liquid
8. Make sure the tip of the needle is in the liquid (see Figure 5). Pull the plunger to withdraw the correct dose into the syringe (see Figure 6).
  Figure 5: Tip in liquid
  Figure 6: Withdraw correct dose
9. Before you take the needle out of the vial, check the syringe for air bubbles. If bubbles are in the syringe, hold the vial and syringe with needle straight up and tap the side of the syringe until the bubbles float to the top. Push the bubbles out with the plunger and draw liquid back in until you have the correct dose (see Figure 7).
  Figure 7: Remove air bubbles and refill syringe
10. Remove the needle from the vial. Do notlet the needle touch anything. You are now ready to inject (see Figure 8).
  Figure 8: Ready to inject

Injecting the Dose:

Inject INCRELEX exactly as your child's doctor or nurse has shown you.

Do not give the INCRELEX injection if your child is unable to eat within 20 minutes before or after the injection.

1. Choose an injection site – upper arm, upper leg (thigh), buttocks, or stomach area (abdomen) (see below). The injection site should be changed (rotated) for each injection.
  Upper arm
  Thigh
  Buttock
  Abdomen
2. Use alcohol to clean the skin where you are going to inject your child. The injection site should be dry before you inject.
  Do notfan or blow on the cleaned skin.
  Do nottouch the injection site again before giving the injection.
3. Lightly pinch the skin. Insert the needle into the pinched skin as instructed by your child's doctor or nurse (see Figure A). Release the pinched skin.
  Figure A: Lightly pinch the skin and inject as instructed
4. Slowly push the plunger of the syringe all the way in to make sure you have injected all of the liquid. Pull the needle straight out and gently press on the injection site with gauze or a cotton ball for a few seconds. Do not rub the injection site(see Figure B).
  Figure B: Press (do notrub) with gauze or cotton ball
5. How should I throw away (dispose of) used needles and syringes?
  - Put used needles and syringes in an FDA-cleared sharps disposal container right away after use. Do not throw away (dispose of) loose needles and syringes in your household trash.
  - Do not try to touch the needle.
  - If you do not have an FDA-cleared sharps disposal container, you may use a household container that is:
    - made of a heavy-duty plastic,
    - can be closed with a tight-fitting, puncture-resistant lid, without sharps being able to come out,
    - upright and stable during use,
    - leak-resistant, and
    - properly labeled to warn of hazardous waste inside the container.
  - When your sharps disposal container is almost full, you will need to follow your community guidelines for the right way to dispose of your sharps disposal container. There may be state or local laws about how to throw away needles and syringes. For more information about safe sharps disposal, and for specific information about sharps disposal in the state that you live in, go to the FDA's website at: http://www.fda.gov/safesharpsdisposal.
  - For the safety and health of you and others, needles and used syringes must neverbe re-used.
  - The used alcohol swabs, cotton balls, and gauze may be placed in your household trash.
  - Do not dispose of your used sharps disposal container in your household trash unless your community guidelines permit this. Do not recycle your used sharps disposal container.
  - Always keep the sharps disposal container out of the reach of children.

How should I store INCRELEX?

- Before Opening: Store new, unopened vials of INCRELEX in the refrigerator between 36°F to 46°F (2°C to 8°C).
- After Opening: Store opened vials of INCRELEX in the refrigerator between 36°F to 46°F (2°C to 8°C) for 30 days after you start using the vial. Throw away any unused INCRELEX after 30 days.
- Do notfreeze INCRELEX. If a vial freezes, throw it away.
- Keep INCRELEX out of direct light.
- Do notuse INCRELEX after the expiration date printed on the label.

Keep INCRELEX and all medicines out of reach of children.

This Instructions for Use has been approved by the U.S. Food and Drug Administration.

For additional information go to https://www.increlex.com or call 1-855-224-0233.

Manufactured by:
Eton Pharmaceuticals, Inc.
21925 W Field Pkwy Ste 235,
Deer Park, IL 60010
U.S. License No. 2393

At:
Simtra Deutschland GmbH
Kantstrasse 2, 33790
Halle (Westfalen), Germany

Revised: 10/2025

PL-23-3.0

PRINCIPAL DISPLAY PANEL - 4 mL Vial Carton and Container

Increlex® (mecasermin) injection 40 mg/4 mL (10 mg/mL) Carton Label

Increlex ® (mecasermin) injection 40 mg/4 mL (10 mg/mL) Container Label